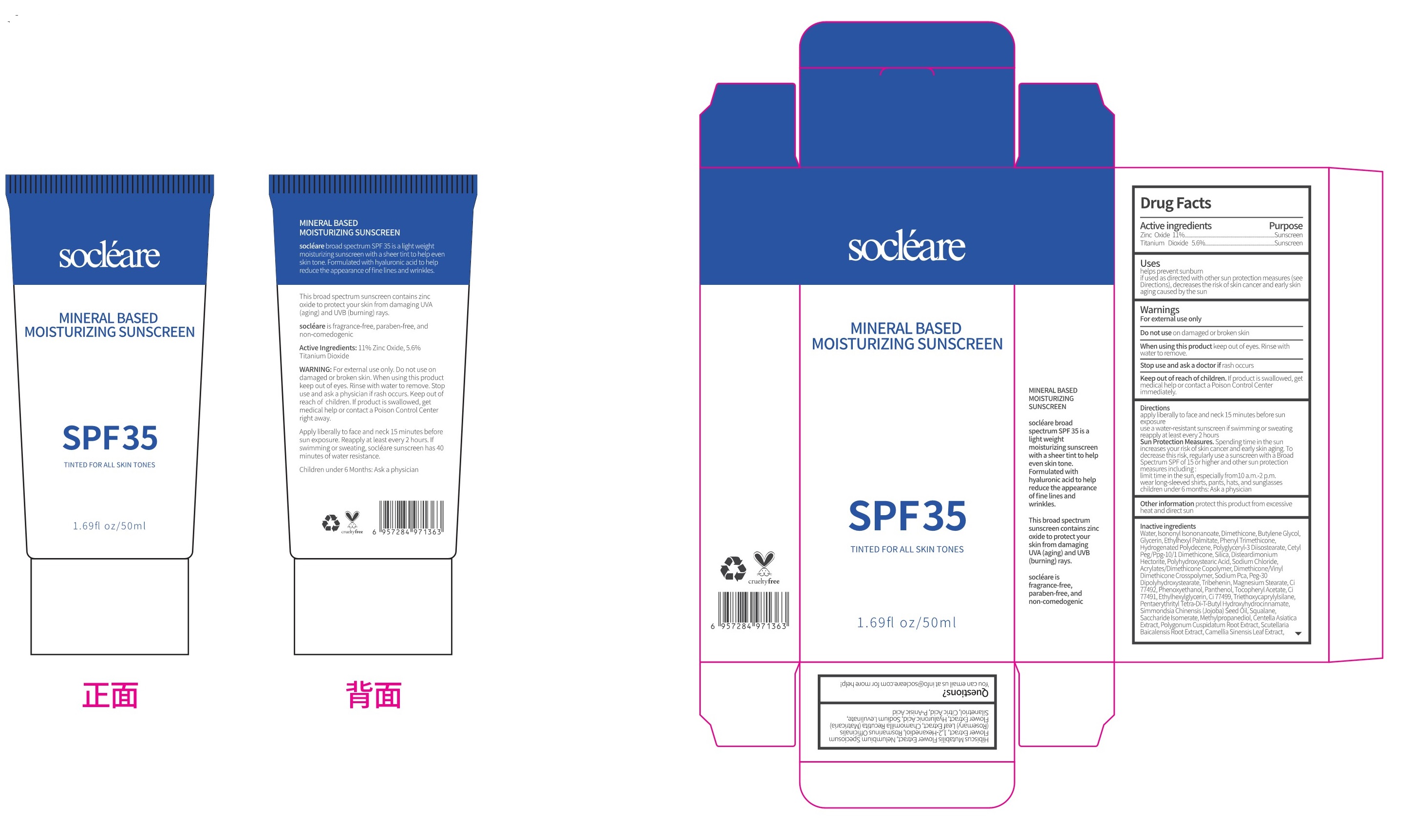 DRUG LABEL: TINTED  FACIAL SUNSCREEN
NDC: 84066-102 | Form: CREAM
Manufacturer: Guangzhou Tata Biotechnology Co., Ltd.
Category: otc | Type: HUMAN OTC DRUG LABEL
Date: 20251222

ACTIVE INGREDIENTS: TITANIUM DIOXIDE 5.6 mg/100 mL; ZINC OXIDE 11 mg/100 mL
INACTIVE INGREDIENTS: ETHYLHEXYL PALMITATE; DIMETHICONE; PHENYL TRIMETHICONE; DISTEARDIMONIUM HECTORITE; SODIUM CHLORIDE; GLYCERIN; HYDROGENATED POLYDECENE (1500 CST); CETYL PEG/PPG-10/1 DIMETHICONE (HLB 3); SODIUM PYRROLIDONE CARBOXYLATE; PANTHENOL; FERRIC OXIDE RED; TRIETHOXYCAPRYLYLSILANE; POLYHYDROXYSTEARIC ACID (2300 MW); MAGNESIUM STEARATE; ETHYLHEXYLGLYCERIN; CENTELLA ASIATICA TRITERPENOIDS; GLYCYRRHIZA GLABRA; HIBISCUS MUTABILIS FLOWER; TRIBEHENIN; FERRIC OXIDE YELLOW; ALPHA-TOCOPHEROL ACETATE; PENTAERYTHRITOL TETRAKIS(3-(3,5-DI-TERT-BUTYL-4-HYDROXYPHENYL)PROPIONATE); JOJOBA OIL; SCUTELLARIA BAICALENSIS ROOT; PRUNUS MUME FLOWER; ROSEMARY; CHAMOMILE; P-ANISIC ACID; BUTYLENE GLYCOL; SILICON DIOXIDE; DIMETHICONE/VINYL DIMETHICONE CROSSPOLYMER (SOFT PARTICLE); SQUALANE; SACCHARIDE ISOMERATE; HYALURONIC ACID; SILANETRIOL; SODIUM LEVULINATE; GREEN TEA LEAF; NELUMBO NUCIFERA FLOWER; 1,2-HEXANEDIOL; POLYGLYCERYL-3 DIISOSTEARATE; 2-ETHYLHEXYL ACRYLATE, METHACRYLATE, METHYL METHACRYLATE, OR BUTYL METHACRYLATE/HYDROXYPROPYL DIMETHICONE COPOLYMER (30000-300000 MW); PEG-30 DIPOLYHYDROXYSTEARATE; PHENOXYETHANOL; FERROSOFERRIC OXIDE; METHYLPROPANEDIOL; POLYGONUM CUSPIDATUM ROOT; PRUNUS PERSICA FLOWER; ISONONYL ISONONANOATE; CITRIC ACID MONOHYDRATE; WATER

TINTED FACIAL SUNSCREEN

ACTIVE INGREDIENT

Zinc Oxide 11%.
Titanium Dioxide 5.6%

PURPOSE

Sunscreen

INDICATIONS AND USAGE

helps prevent sunburnifused as directed with other sun protection measures (seeDirections),decreases the risk of skin cancer and early skinaging caused by the sun

WARNINGS

For external use only

Do not use on damaged or broken skin

When using this product keep out of eyes. Rinse with water to remove.

Stop use and ask a doctor if rash occurs.

Keep out of reach of children. If product is swallowed, get medical help or contact a Poison Control Center right away.

Directions
apply liberally 15 minutes before sun exposure
reapply: after 80 minutes of swimming or sweating
immediately after towel drying at least every 2 hours
children under 6 months of age: ask a doctor Sun Protection Measures. Spendingtime in the sun increases your risk of skin cancer and early skin aging
thisrisk, regularly use a sunscreen with a Broad Spertrum SPF of 15 or higher
limit time in the sun, especially from 10 a.m.-2 p.m.
wear long-sleeved shirts,pants,hats and sunglasses.

Children under 6 months of age : Ask a doctor.

OTHER SAFETY INFORMATION

Protect the product in this container from excessive heat and direct sun

INACTIVE INGREDIENT

Water, lsononyl lsononanoate, Dimethicone, Butylene GlycolGlycerin, Ethylhexyl Palmitate, Phenyl Trimethicone,Hydrogenated Polydecene, Polyglyceryl-3 Diisostearate, CetyPeg/Ppg-10/1 Dimethicone, Silica, DisteardimoniumHectorite, Polyhydroxystearic Acid, Sodium Chloride.Acrylates/Dimethicone Copolymer, Dimethicone/VinylDimethicone Crosspolymer, Sodium Pca, Peg-30Dipolyhydroxystearate, Tribehenin, Magnesium Stearate, Ci77492,Phenoxyethanol, Panthenol, Tocopheryl Acetate, Ci77491, Ethylhexylglycerin, Ci77499, Triethoxycaprylylsilane,PentaerythritylTetra-Di-T-Butyl Hydroxyhydrocinnamate,Simmondsia Chinensis (Jojoba) Seed Oil, Squalane.Saccharide lsomerate, Methylpropanediol, Centella AsiaticaExtract, Polygonum Cuspidatum Root Extract, ScutellariaBaicalensis Root Extract, Camellia Sinensis Leaf Extract,Hibiscus Mutabilis Flower Extract,Nelumbium SpeciosumFlower Extract,1.2-Hexanediol,Rosmarinus Officinalis(Rosemary) Leaf Extract, Chamomilla Recutita (MatricariaFlower Exiract, Hyaluronic Acid, Sodium Levulinate,Silanetriol, Citric Acid, P-Anisic Acid

QUESTIONS

You can email us at info@socleare.com for more help!